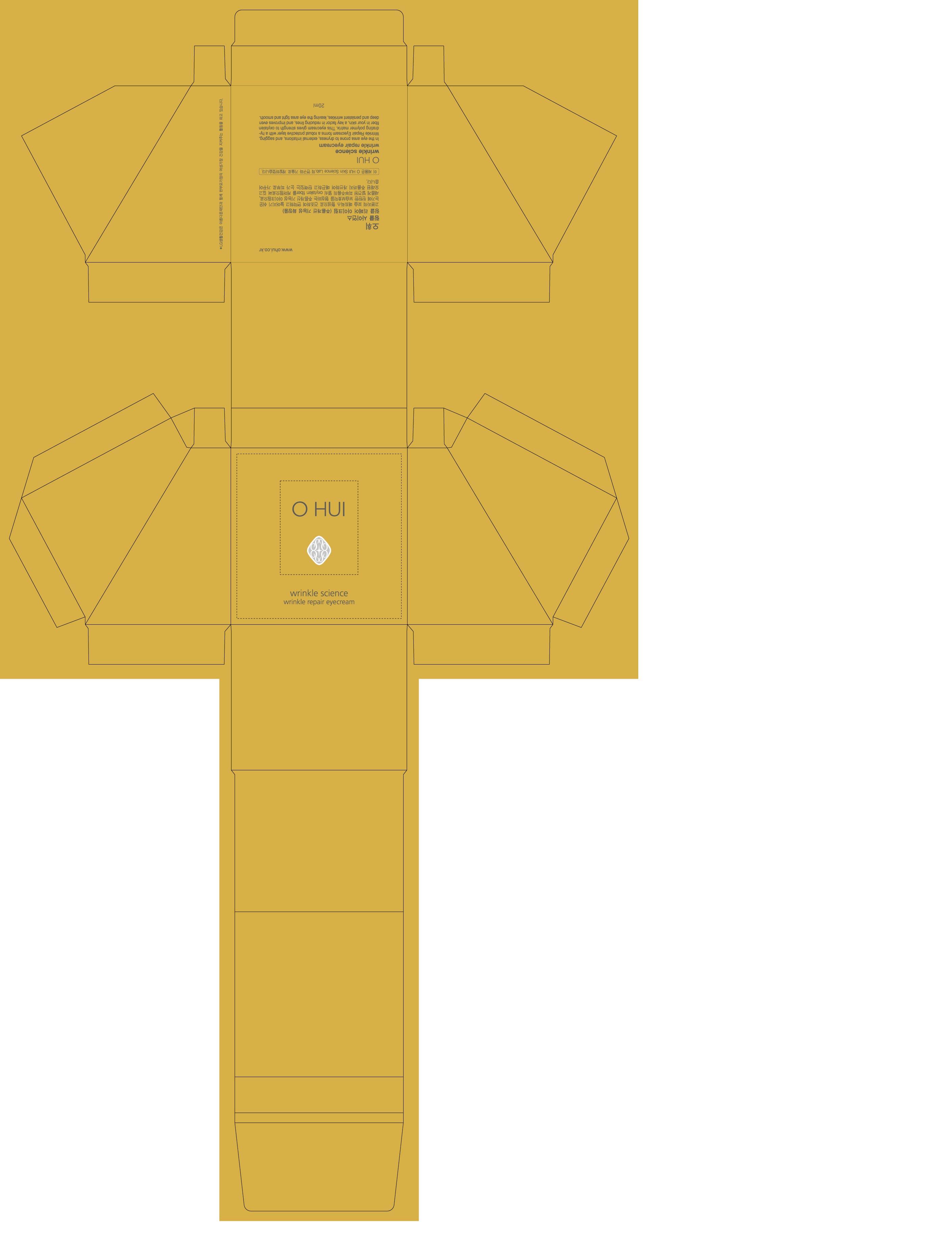 DRUG LABEL: OHUI Wrinkle Science wrinkle repair eye 
NDC: 53208-429 | Form: CREAM
Manufacturer: LG Household and Healthcare, Inc.
Category: otc | Type: HUMAN OTC DRUG LABEL
Date: 20100604

ACTIVE INGREDIENTS: HYDROXYPROLINE 0.51 1/100 mL
INACTIVE INGREDIENTS: WATER; GLYCERIN; DIPROPYLENE GLYCOL; CYCLOMETHICONE 5; CAPRYLIC/CAPRIC MONO/DIGLYCERIDES; SHEA BUTTER; CAPRIC ACID; GLYCERYL MONOSTEARATE; CETOSTEARYL ALCOHOL; PANTHENOL; SORBITAN MONOSTEARATE; YELLOW wax; DIMETHICONE; METHYLPARABEN; ALPHA-TOCOPHEROL; PROPYLPARABEN; TROLAMINE; ETHYLPARABEN; EDETATE TRISODIUM; FD&C YELLOW NO. 6; FD&C YELLOW NO. 5

DRUG FACTS

ACTIVE INGREDIENTS

HYDROXYPROLINE 0.51mL/100mL

WARNING AND PRECAUTIONS

For external use only.

Keep out of reach of children. Is swallowed, get medical help or contact a Poison Control Center right away.

WHEN USING

Keep out of eyes. Rinse with water to remove.

STOP USE

Stop use if a rash or irritation develops and lasts.

PACKAGE LABEL

OHUI

WRINKLE SCIENCE

EYE CREAM